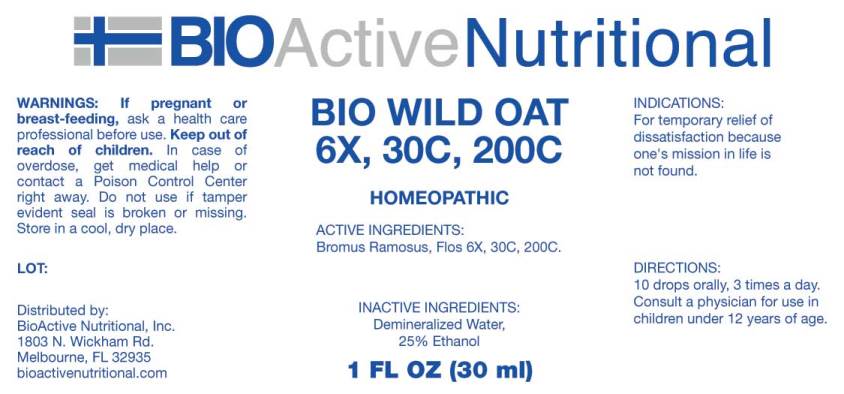 DRUG LABEL: Bio Wild Oat
NDC: 43857-0182 | Form: LIQUID
Manufacturer: BioActive Nutritional, Inc.
Category: homeopathic | Type: HUMAN OTC DRUG LABEL
Date: 20171129

ACTIVE INGREDIENTS: BROMUS RAMOSUS FLOWER 6 [hp_X]/1 mL
INACTIVE INGREDIENTS: WATER; ALCOHOL

Drug Facts:

ACTIVE INGREDIENTS:

Wild Oat 6X, 30C, 200C.

INDICATIONS:

For temporary relief of dissatisfaction because one's mission in life is not found.

WARNINGS

If pregnant or breast-feeding, ask a health care professional before use.

Keep out of reach of children. In case of overdose, get medical help or contact a Poison Control Center right away.

Do not use if tamper evident seal is broken or missing.

Store in cool, dry place.

DIRECTIONS:

10 drops orally, 3 times a day. Consult a physician for use in children under 12 years of age.

INACTIVE INGREDIENTS:

Demineralized Water, 25% Ethanol.

Keep out of reach of children. In case of overdose, get medical help or contact a Poison Control Center right away.

INDICATIONS:

For temporary relief of dissatisfaction because one's mission in life is not found.

QUESTIONS

Distributed by:
BioActive Nutritional, Inc.
1803 N. Wickham Rd.
Melbourne, FL 32935
bioactivenutritional.com

PACKAGE DISPLAY LABEL:

BIOActive Nutritional

BIO WILD OAT

6X, 30C, 200C

HOMEOPATHIC

1 FL OZ (30 ml)